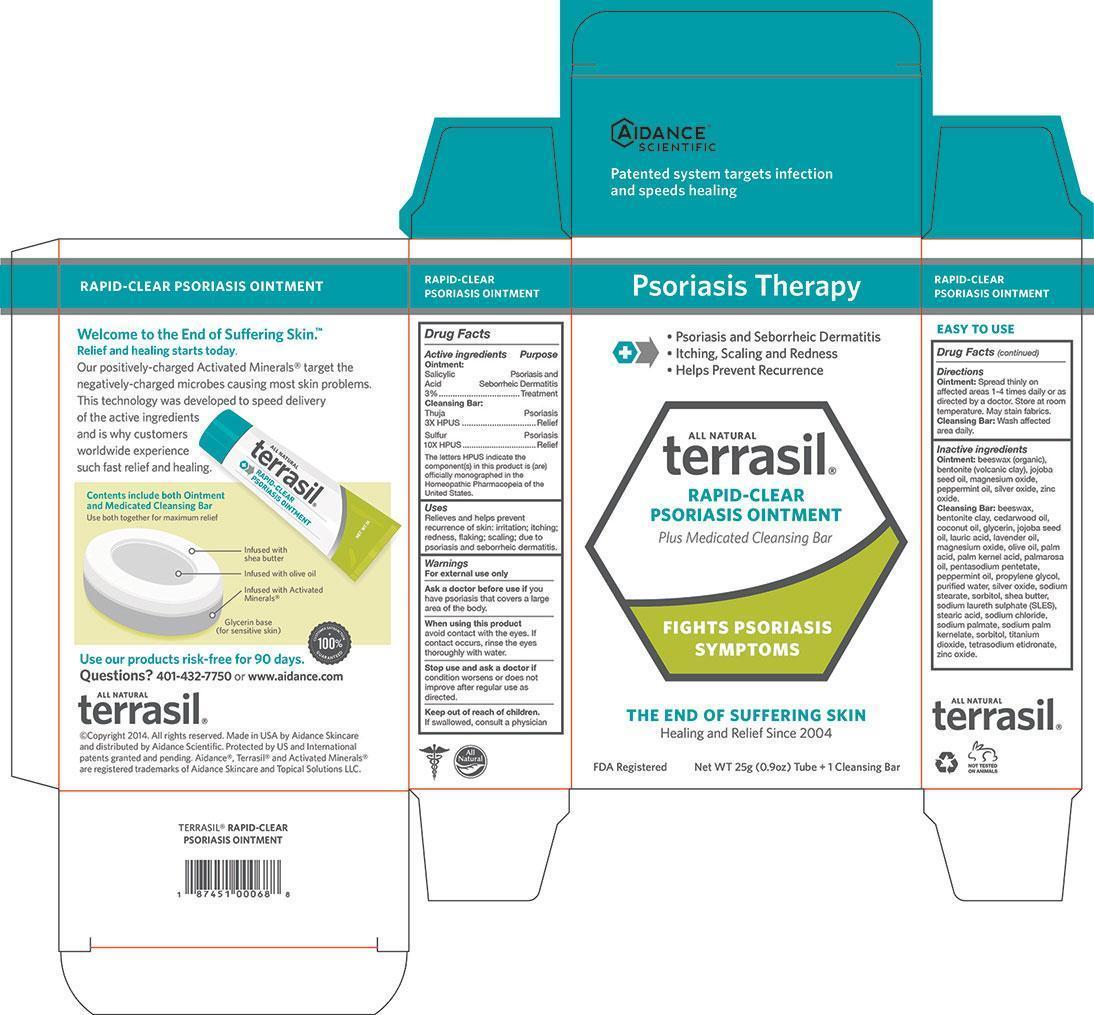 DRUG LABEL: Terrasil Rapid-Clear Psoriasis
NDC: 24909-164 | Form: KIT | Route: TOPICAL
Manufacturer: Aidance Skincare & Topical Solutions, LLC
Category: otc | Type: HUMAN OTC DRUG LABEL
Date: 20140418

ACTIVE INGREDIENTS: SALICYLIC ACID 3 g/100 g; THUJA OCCIDENTALIS LEAFY TWIG 3 [hp_X]/1 g; SULFUR 10 [hp_X]/1 g
INACTIVE INGREDIENTS: BENTONITE; JOJOBA OIL; MAGNESIUM OXIDE; PEPPERMINT OIL; SILVER OXIDE; WHITE WAX; ZINC OXIDE; BENTONITE; CEDAR LEAF OIL; COCONUT OIL; GLYCERIN; JOJOBA OIL; LAURIC ACID; LAVENDER OIL; MAGNESIUM OXIDE; OLIVE OIL; PALM ACID; PALM KERNEL ACID; PENTASODIUM PENTETATE; PEPPERMINT OIL; PROPYLENE GLYCOL; SILVER OXIDE; SODIUM STEARATE; SHEA BUTTER; SODIUM LAURETH SULFATE; STEARIC ACID; SODIUM CHLORIDE; SODIUM PALMATE; SODIUM PALM KERNELATE; SORBITOL; TITANIUM DIOXIDE; ETIDRONATE TETRASODIUM; WATER; WHITE WAX; ZINC OXIDE

Drug Facts

Active Ingredient

Ointment: Salicylic Acid 3%
Cleansing Bar: Thuja 3X HPUS, Sulfur 10X HPUS
The letters HPUS indicate the component(s) in this product is (are) officially monographed in the Homeopathic Pharmacopeia of the United States

Purpose

Salicylic Acid - Psoriasis and Seborrheic Dermatitis Treatment
Thuja, Sulfur - Psoriasis Relief

Uses

Relieves and helps prevent recurrence of skin: irritation; itching;
redness, flaking; scaling; due to psoriasis and seborrheic dermatitis.

Warnings

For external use only

Ask a doctor before use if you have psoriasis that covers a large area of the body.
When using this product avoid contact with the eyes. If contact occurs, rinse the eyes
thoroughly with water.
Stop use and ask a doctor if condition worsens or does not improve after regular use as directed.

Keep out of reach of children.

If swallowed, consult a physician.

Directions

Ointment: Spread thinly on affected areas 1-4 times daily or as directed by a doctor.
Store at room temperature. May stain fabrics.
Cleansing Bar: Wash affected area daily.

Inactive Ingredients

Ointment: beeswax (organic), bentonite (volcanic clay), jojoba seed oil, magnesium oxide, peppermint oil, silver oxide, zinc oxide.

Cleansing Bar: beeswax, bentonite clay, cedarwood oil, coconut oil, glycerin, jojoba seed oil, lauric acid, lavender oil, magnesium oxide, olive oil, palm acid, palm kernel acid, pentasodium pentetate, peppermint oil, propylene glycol, purified water, silver oxide, sodium stearate, sorbitol, shea butter, sodium laureth sulphate (SLES), stearic acid, sodium chloride, sodium palmate, sodium palm kernelate, sorbitol, titanium dioxide, tetrasodium etidronate, zinc oxide.

PRINCIPAL DISPLAY PANEL - BOX

Psoriasis Therapy

- Psoriasis and Seborrheic Dermatitis
- Itching, Scaling and Redness
- Helps Prevent Recurrence

All Natural

terrasil

RAPID-CLEAR PSORIASIS OINTMENT

Plus Medicated Cleansing Bar

FIGHTS PSORIASIS SYMPTOMS

THE END OF SUFFERING SKIN

Healing and Relief Since 2004